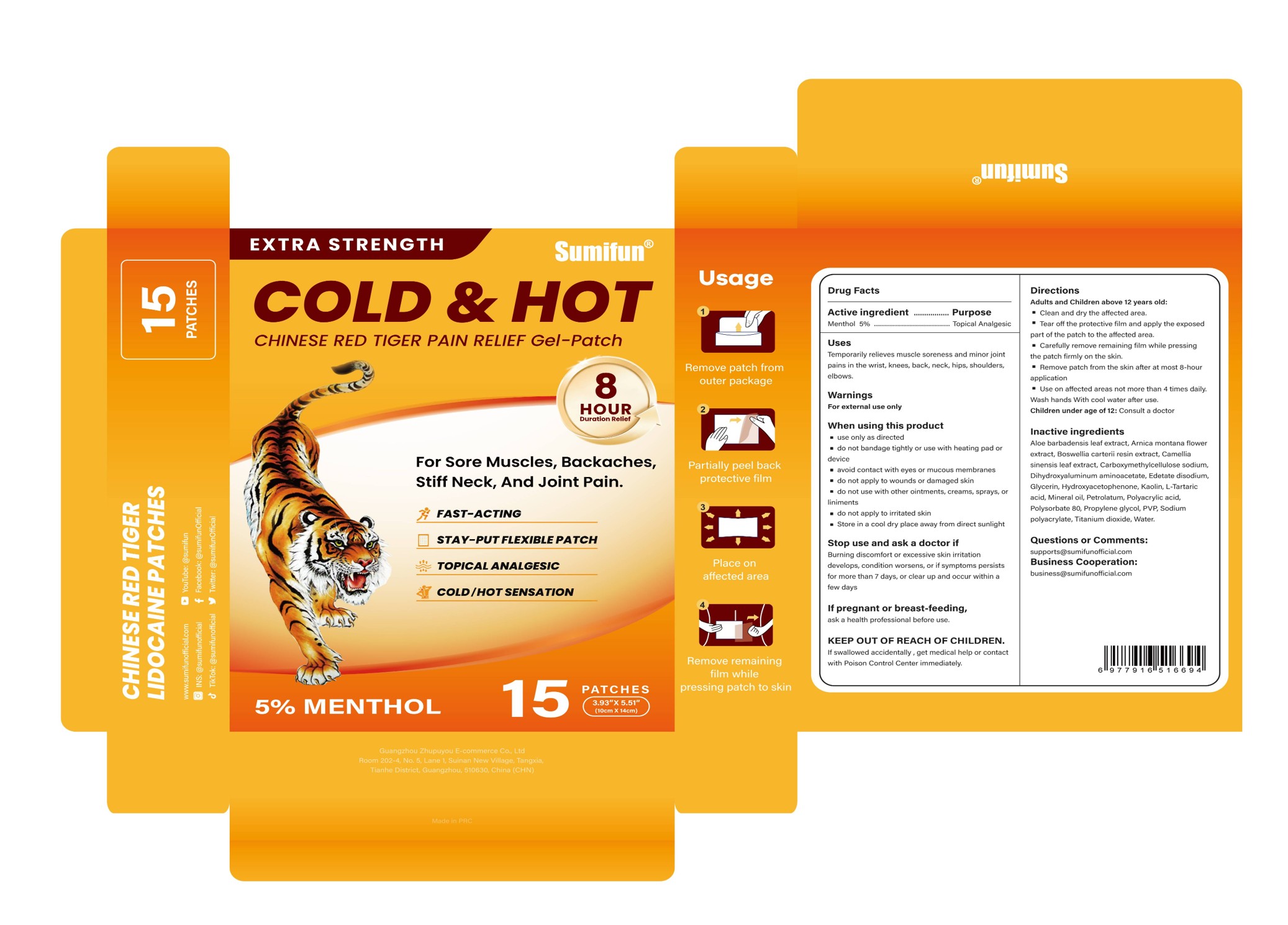 DRUG LABEL: COLD HOT CHINESE RED TIGER PAIN RELIEF GeI-Patch
NDC: 84165-004 | Form: PATCH
Manufacturer: Guangzhou Zhupuyou E-commerce Co., Ltd
Category: otc | Type: HUMAN OTC DRUG LABEL
Date: 20250414

ACTIVE INGREDIENTS: MENTHOL 0.05 g/1 g
INACTIVE INGREDIENTS: DIHYDROXYALUMINUM AMINOACETATE ANHYDROUS; ALOE BARBADENSIS LEAF; HYDROXYACETOPHENONE; POLYSORBATE 80; TARTARIC ACID; TITANIUM DIOXIDE; EDETATE DISODIUM; PROPYLENE GLYCOL; MINERAL OIL; GLYCERIN; KAOLIN; SODIUM POLYACRYLATE (2500000 MW); ARNICA MONTANA FLOWER; FRANKINCENSE; CAMELLIA SINENSIS LEAF; CARBOXYMETHYLCELLULOSE SODIUM; PETROLATUM; POLYACRYLIC ACID (250000 MW); POVIDONE K90; WATER

COLD & HOT CHINESE RED TIGER PAIN RELIEF GeI-Patch

ACTIVE INGREDIENT

Menthol

PURPOSE

Topical Analgesic

INDICATIONS AND USAGE

Temporarily relieves muscle soreness and minor jointpains in the wrist, knees, back, neck, hips, shoulders,elbows.

WARNINGS

For external use only

WHEN USING

use only as directed
do not bandage tightly or use with heating pad ordevice
avoid contact with eyes or mucous membranes
do not apply to wounds or damaged skin
do not use with other ointments, creams, sprays, orliniments
do not apply to irritated skin
Store in a cool dry place away from direct sunlight

STOP USE

Buring discomfort or excessive skin irritationdevelops, condition worsens, or if symptoms persistsfor more than 7 days, or clear up and occur within afew days

KEEP OUT OF REACH OF CHILDREN

If swallowed accidentally , get medical help or contactwith Poison Control Center immediately.

DOSAGE AND ADMINISTRATION

Adults and Children above 12 years old:
Clean and dry the affected area.
Tear off the protective film and apply the exposedpart of the patch to the affected area.
Carefully remove remaining film while pressingthe patch firmly on the skin.
Remove patch from the skin after at most 8-hour application
Use on affected areas not more than 4 times dailyWash hands With cool water after use.
Children under age of 12: Consult a doctor

INACTIVE INGREDIENT

Aloe Barbadensis Leaf Extract
Arnica Montana Flower Extract
Boswellia Carterii Resin Extract
Camellia Sinensis Leaf Extract
Carboxymethylcellulose Sodium
Dihydroxyaluminum Aminoacetate
Edetate Disodium
Glycerin
Hydroxyacetophenone
Kaolin
L-Tartaric Acid
Mineral Oil
Petrolatum
Polyacrylic Acid
Polysorbate 80
Propylene Glycol
PVP
Sodium Polyacrylate
Titanium Dioxide
Water